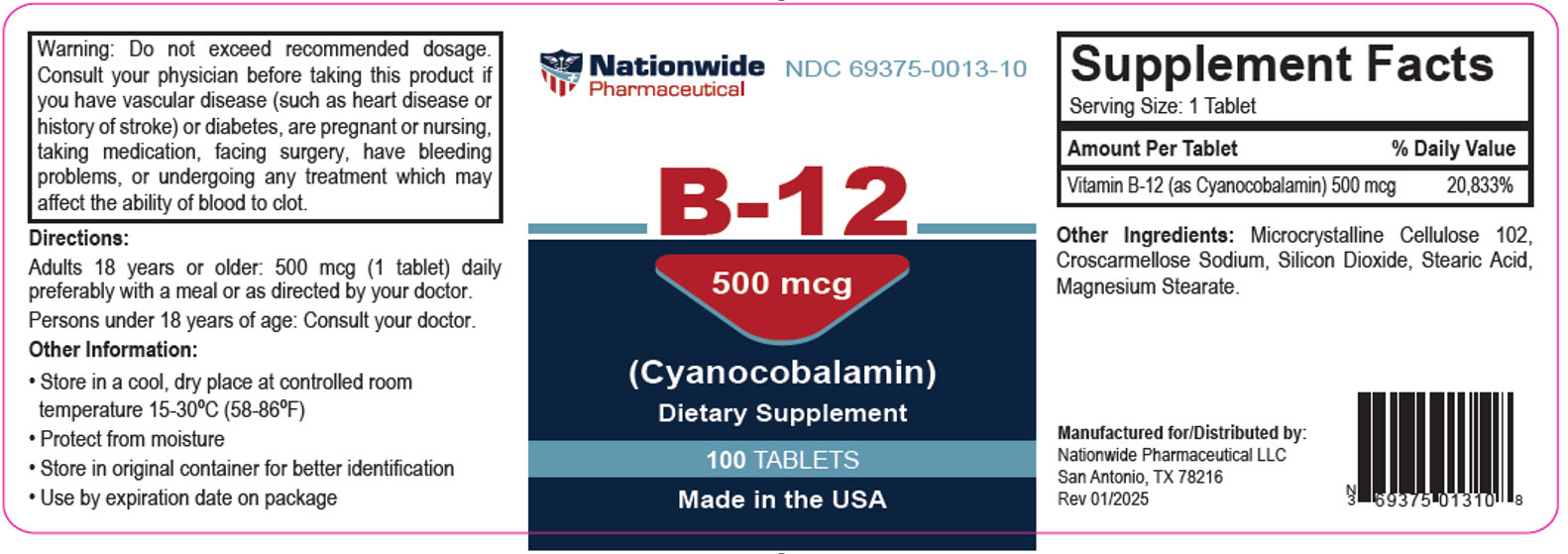 DRUG LABEL: B-12 (Cyanocobalamin)
NDC: 69375-013 | Form: TABLET
Manufacturer: Nationwide Pharmaceutical LLC
Category: other | Type: DIETARY SUPPLEMENT
Date: 20250219

ACTIVE INGREDIENTS: Cyanocobalamin 500 ug/1 1
INACTIVE INGREDIENTS: Microcrystalline Cellulose 102; Croscarmellose sodium; Silicon Dioxide; Stearic Acid; Magnesium stearate

B-12 (Cyanocobalamin)

WARNINGS

Warning: Do not exceed recommended dosage. Consult your physician before taking this product if you have vascular disease (such as heart disease or history of stroke) or diabetes, are pregnant or nursing, taking medication, facing surgery, have bleeding problems, or undergoing any treatment which may affect the ability of blood to clot.

Directions

Adults 18 years or older: 500 mcg (1 tablet) daily preferably with a meal or as directed by your doctor.

Persons under 18 years of age: Consult your doctor.

Other Information

- Store in a cool, dry place at controlled room termperature 15-30°C (58-86°F)
- Protect from moisture
- Store in original container for better identification
- Use by expiration date on package

STATEMENT OF IDENTITY

Supplement Facts

Serving Size: 1 Tablet

Amount Per Tablet

% Daily Value

Vitamin B-12 (as Cyanocobalamin)

500 mcg

20,833%

Other Ingredients: Microcrystalline Cellulose 102, Croscarmellose Sodium, Silicon Dioxide, Stearic Acid, Magnesium Stearate

HEALTH CLAIM

Manufactured for/Distributed by:
Nationwide Pharmaceutical LLC
San Antonio, TX 78216
Rev 1/2025

PRINCIPAL DISPLAY PANEL - 500 mcg Tablet Bottle Label

Nationwide
Pharmaceutical
NDC 69375-0013-10

B-12

500 mcg

(Cyanocobalamin)

100 TABLETS

Made in the USA